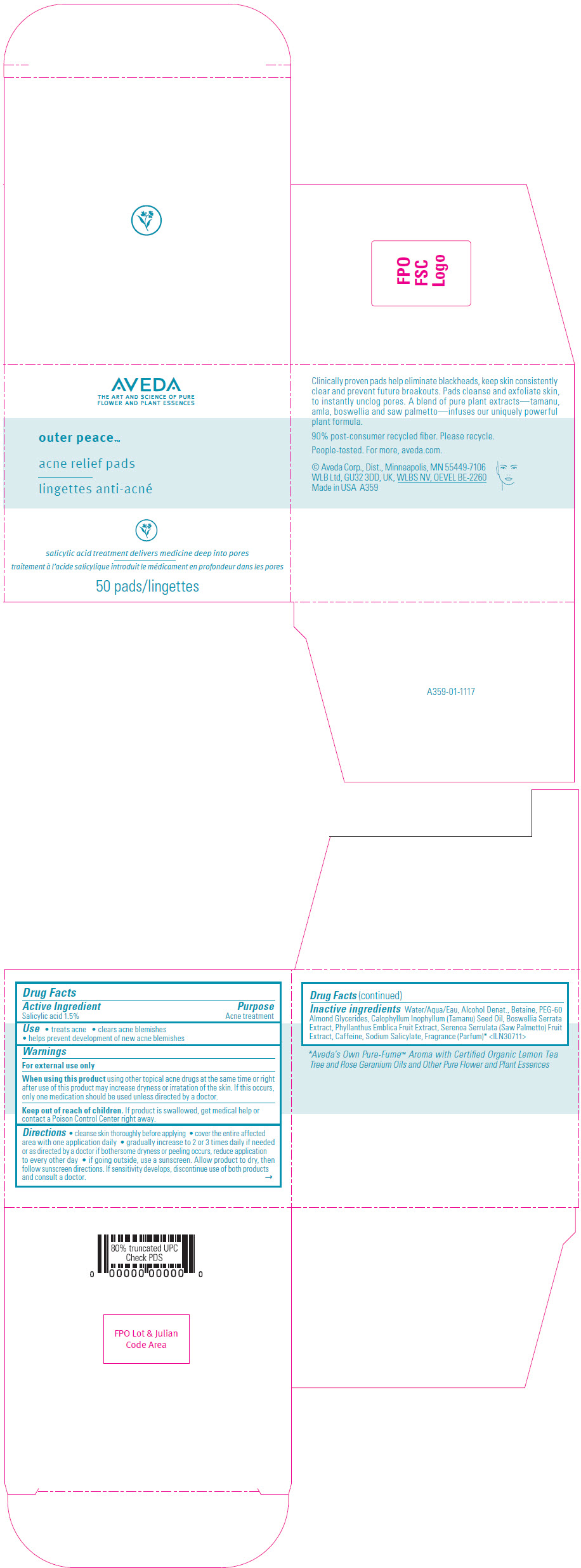 DRUG LABEL: AVEDA OUTER PEACE ACNE RELIEF PADS
NDC: 57677-064 | Form: SOLUTION
Manufacturer: Aveda Corporation
Category: otc | Type: HUMAN OTC DRUG LABEL
Date: 20241115

ACTIVE INGREDIENTS: SALICYLIC ACID 15 mg/1 g
INACTIVE INGREDIENTS: WATER; ALCOHOL; BETAINE; PEG-60 ALMOND GLYCERIDES; TAMANU OIL; INDIAN FRANKINCENSE; PHYLLANTHUS EMBLICA FRUIT; SAW PALMETTO; CAFFEINE; SODIUM SALICYLATE; FRAGRANCE CLEAN ORC0600327

AVEDA OUTER PEACE™ ACNE RELIEF PADS

Drug Facts

Active Ingredient

Salicylic acid 1.5%

Purpose

Acne treatment

Use

- treats acne
- clears acne blemishes
- helps prevent development of new acne blemishes

Warnings

For external use only

When using this product using other topical acne drugs at the same time or right after use of this product may increase dryness or irritation of the skin. If this occurs, only one medication should be used unless directed by a doctor.

Keep out of reach of children. If product is swallowed, get medical help or contact a Poison Control Center right away.

Directions

- cleanse skin thoroughly before applying
- cover the entire affected area with one application daily
- gradually increase to 2 or 3 times daily if needed or as directed by a doctor if bothersome dryness or peeling occurs, reduce application to every other day
- if going outside, use a sunscreen. Allow product to dry, then follow sunscreen directions. If sensitivity develops, discontinue use of both products and consult a doctor.

Inactive ingredients

Water/Aqua/Eau, Alcohol Denat., Betaine, PEG-60 Almond Glycerides, Calophyllum Inophyllum (Tamanu) Seed Oil, Boswellia Serrata Extract, Phyllanthus Emblica Fruit Extract, Serenoa Serrulata (Saw Palmetto) Fruit Extract, Caffeine, Sodium Salicylate, Fragrance (Parfum) [Aveda's Own Pure-Fume™ Aroma with Certified Organic Lemon Tea Tree and Rose Geranium Oils and Other Pure Flower and Plant Essences] <ILN30711>

PRINCIPAL DISPLAY PANEL - 50 Pad Jar Carton

AVEDA
THE ART AND SCIENCE OF PURE
FLOWER AND PLANT ESSENCES

outer peace™

acne relief pads

salicylic acid treatment delivers medicine deep into pores

50 pads